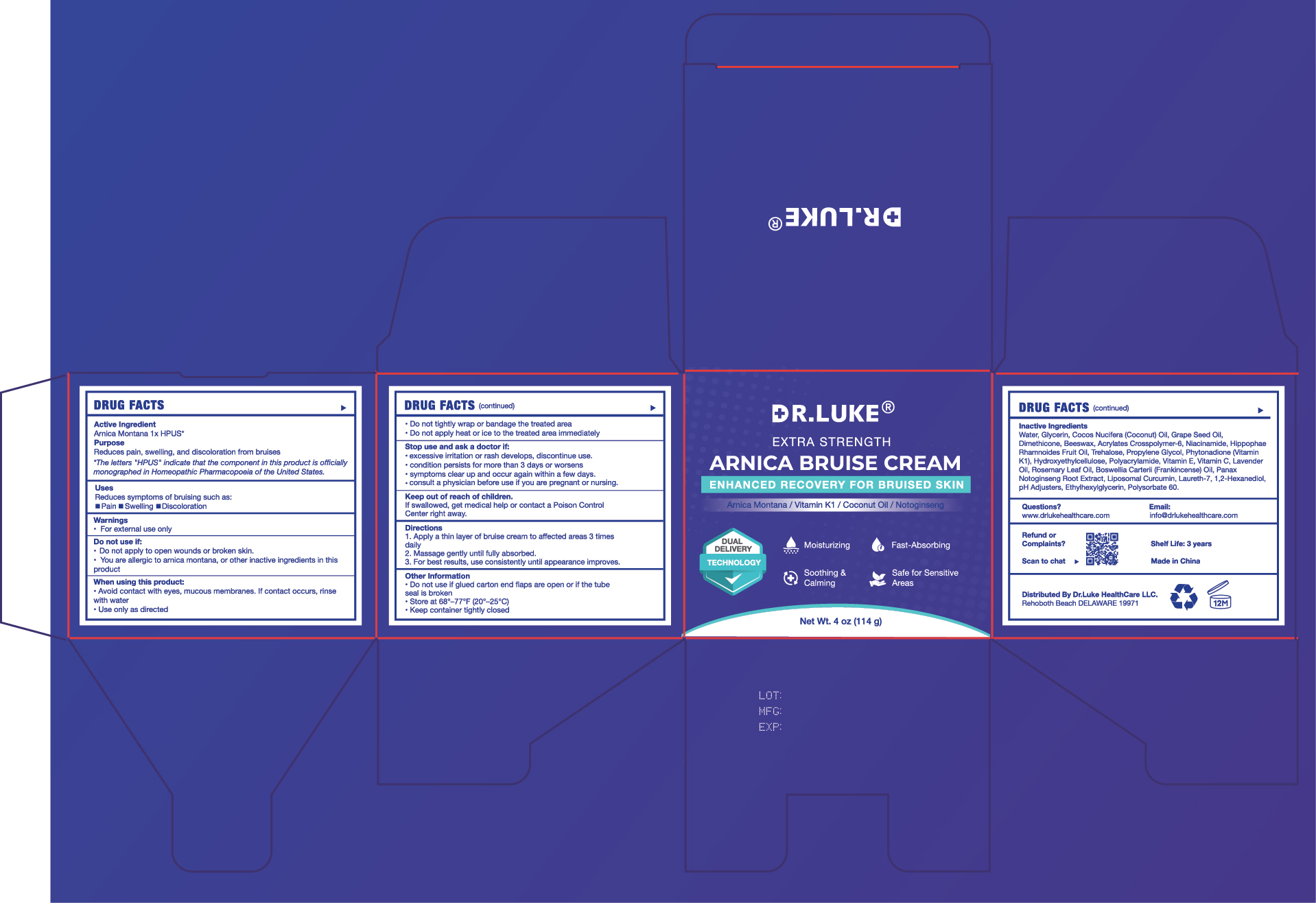 DRUG LABEL: Dr. Luke Arnica Bruise Cream
NDC: 87147-004 | Form: CREAM
Manufacturer: DANOUS LAND FLOOW LLC
Category: otc | Type: HUMAN OTC DRUG LABEL
Date: 20251013

ACTIVE INGREDIENTS: ARNICA MONTANA WHOLE 5 g/100 g
INACTIVE INGREDIENTS: ALPHA-TOCOPHEROL; WATER; GLYCERIN; COCOS NUCIFERA (COCONUT) OIL; GRAPE SEED OIL; DIMETHICONE; BEESWAX; NIACINAMIDE; HIPPOPHAE RHAMNOIDES FRUIT OIL; TREHALOSE; PROPYLENE GLYCOL; PHYTONADIONE; LAVENDER OIL; HYDROXYETHYLCELLULOSE

ACTIVE INGREDIENT

Arnica Montana 1x HPUS

PURPOSE

Reduces pain, swelling, and discoloration from bruises

WHEN USING

Avoid contact with eyes, mucous membranes. If contact occurs, rinse with water.
Use only as directed
Do not tightly wrap or bandage the treated area.
Do not apply heat or ice to the treated area immediately.

DO NOT USE

Do not apply to open wounds or broken skin.
You are allergic to arnica montana, or other inactive ingredients in this product

KEEP OUT OF REACH OF CHILDREN

If swallowed, get medical help or contact a Poison Control Center right away.

WARNINGS

For external use only.

INACTIVE INGREDIENT

Water, Glycerin, Cocos Nucifera (Coconut) Oil, Grape Seed Oil,Dimethicone, Beeswax, Acrylates Crosspolymer-6, Niacinamide, Hippophae
Rhamnoides Fruit Oil, Trehalose, Propylene Glycol, Phytonadione (Vitamin
K1), Hydroxyethylcellulose, Polyacrylamide, Vitamin E, Vitamin C, Lavender
Oil, Rosemary Leaf Oil, Boswellia Carterii (Frankincense) Oil, Panax
Notoginseng Root Extract, Liposomal Curcumin, Laureth-7, 1,2-Hexanediol,
pH Adjusters, Ethylhexylglycerin, Polysorbate 60.

INSTRUCTIONS FOR USE

Apply a thin layer of bruise cream to affected areas 3 times daily.
Massage gently until fully absorbed.
For best results, use consistently until appearance improves.

INDICATIONS AND USAGE

Reduces symptoms of bruising such as: Pain, Swelling, Discoloration

DOSAGE AND ADMINISTRATION

Apply to affected area not more than 3–4 times daily.

Do not use if glued carton end flaps are open or if the tube seal is broken.
Store at 68°-77°F (20°-25C).
Keep container tightly closed